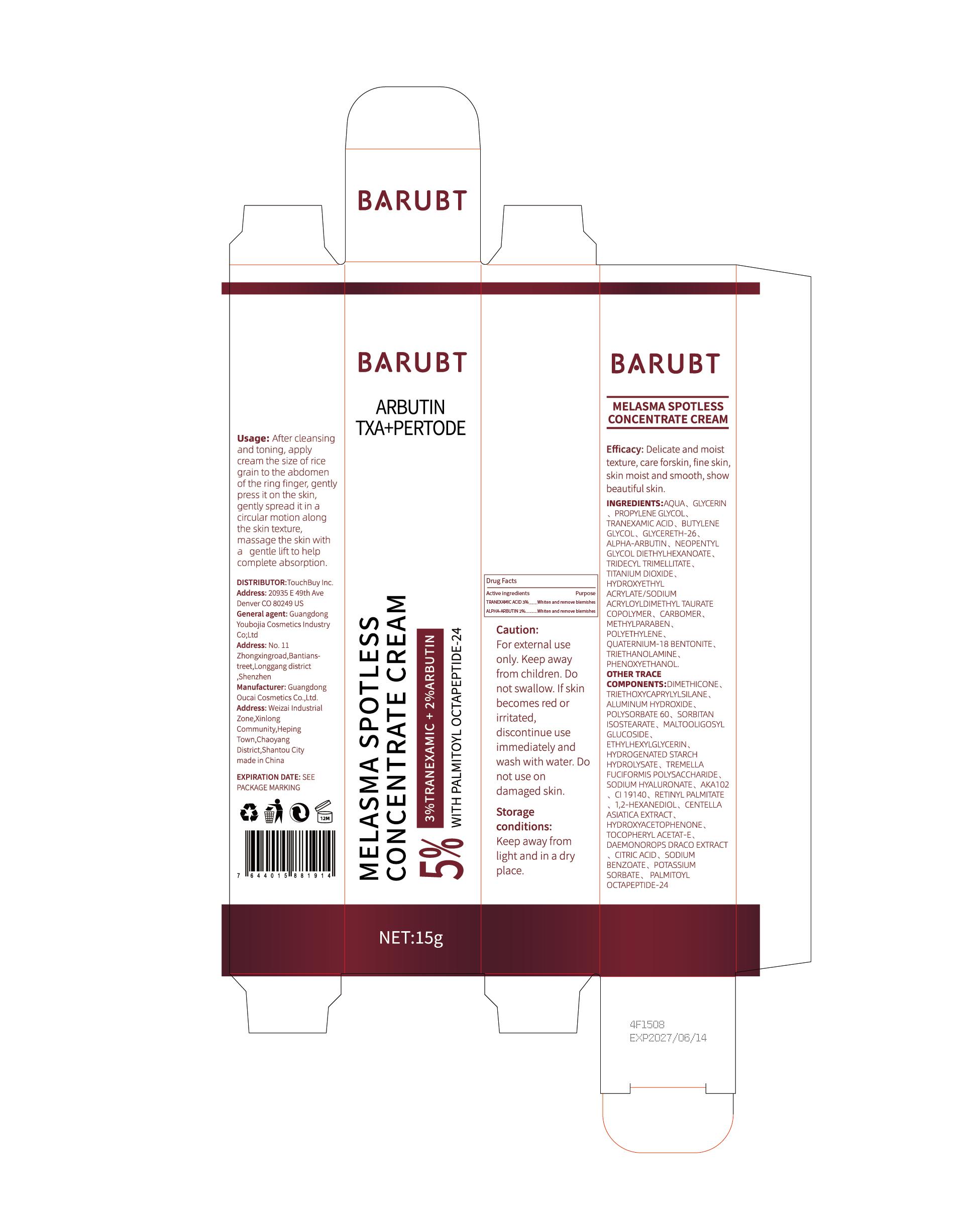 DRUG LABEL: BARUBT Melasma spotless concentrate cream
NDC: 84712-002 | Form: CREAM
Manufacturer: Guangdong Youbaijia Cosmetic Industry Co., Ltd
Category: otc | Type: HUMAN OTC DRUG LABEL
Date: 20240908

ACTIVE INGREDIENTS: TRANEXAMIC ACID 0.45 g/15 g; ALPHA-ARBUTIN 0.3 g/15 g
INACTIVE INGREDIENTS: NEOPENTYL GLYCOL DIETHYLHEXANOATE 0.15 g/15 g; BUTYLENE GLYCOL 0.3 g/15 g; GLYCERETH-26 0.3 g/15 g; TRIDECYL TRIMELLITATE 0.15 g/15 g; GLYCERIN 0.75 g/15 g

Active Ingredient

TRANEXAMIC ACID 3%
ALPHA-ARBUTIN 2%

Purpose

Melasma spotless

Usage

After dleansing the skin, take an appropriate amount of this product and apply it evenly on the skin. Massage gently until absorbed. For best results, it is recommended to use three times a week.

Warnings

For external use only. Keep out of reach of children. Avoid contact with E. If you show signs of irritation or rash, stop using.

Stop use

If you show signs of irritation or rash, stop using.

Do not use

on damaged or broken shin

keep out of reach of children

If swallowed, get medical help or contact a Poison Control Center right away.

Using

keep out of eyes. Rinse with water to remove

Inactive ingredients

AQUA
GLYCERIN
PROPYLENE GLYCOL
BUTYLENE GLYCOL
GLYCERETH-26
NEOPENTYLGLYCOL DIETHYLHEXANOATE
TRIDECYL TRIMELLITATE
TITANIUM DIOXIDE
HYDROXYETHYL ACRYLATE/SODIUM ACRYLOYLDIMETHYL TAURATE COPOLYMER
CARBOMER
POLYETHYLENE
QUATERNIUM-18 BENTONITE
TRIETHANOLAMINE
PHENOXYETHANOL
METHYLPARABEN
DIMETHICONE
TRIETHOXYCAPRYLYLSILANE
ALUMINUM HYDROXIDE
POLYSORBATE 60
SORBITAN ISOSTEARATE
MALTOOLIGOSYL GLUCOSIDE
ETHYLHEXYLGLYCERIN
HYDROGENATED STARCH HYDROLYSATE
TREMELLA FUCIFORMIS POLYSACCHARIDE
SODIUM HYALURONATE
AKA102
CI19140
RETINYL PALMITATE
1,2-HEXANEDIOL
CENTELLA ASIATICA EXTRACT
HYDROXYACETOPHENONE
TOCOPHERYL ACETAT-E
DAEMONOROPS DRACO EXTRACT CITRIC ACID
SODIUM BENZOATE
POTASSIUM SORBATE
PALMITOYL OCTAPEPTIDE-24

Storage

Store in a cool and dry place.

QUESTIONS

Companyphonenumber: 1-510-671-4443
Companye-mail: cpnpmrlin@gmail.com

DOSAGE AND ADMINISTRATION

- well cleansing your face
- apply mean brightening cream to face and massage until completely absorbed.
- children under 6 months ofage: Ask a doctor